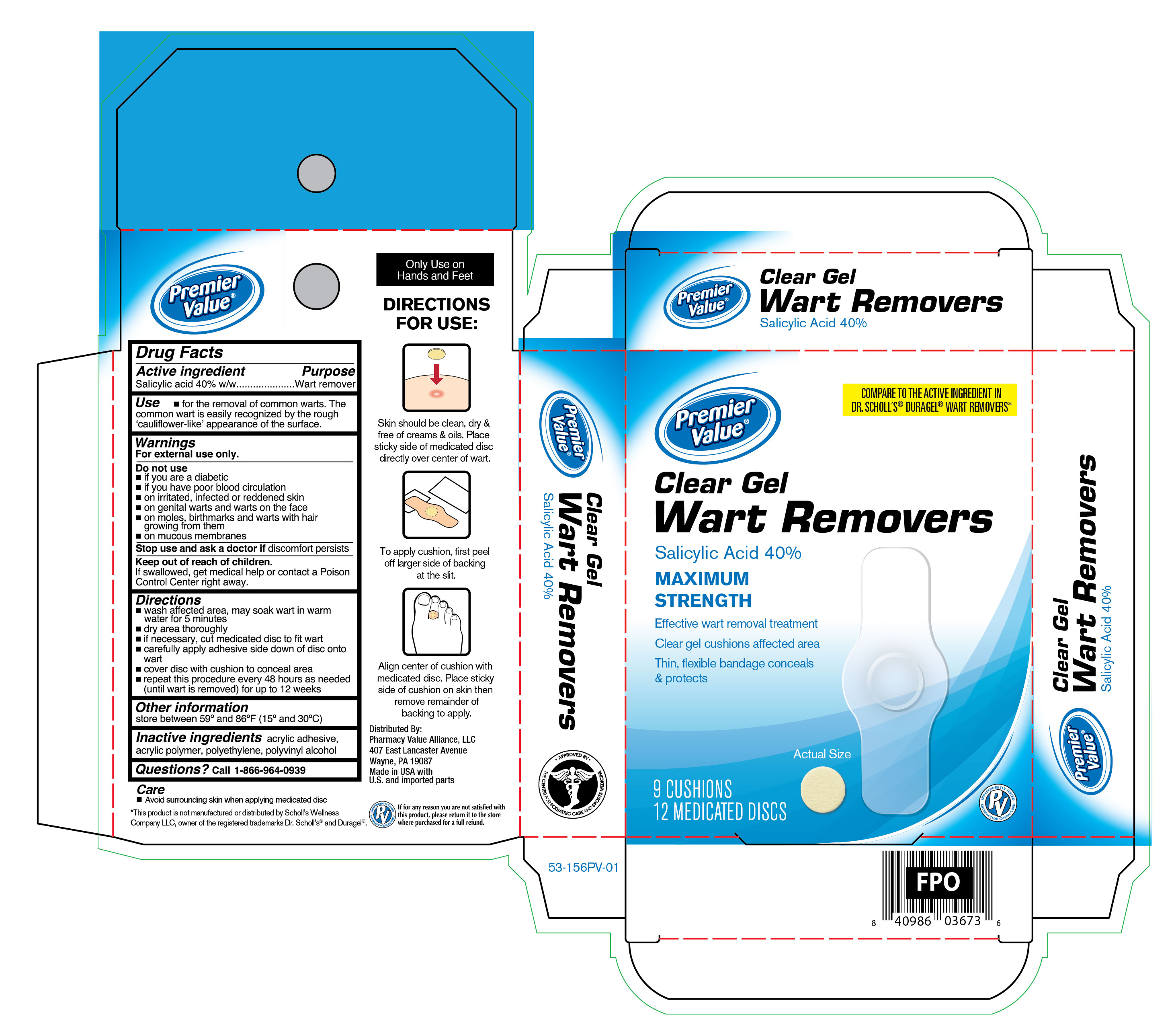 DRUG LABEL: Clear Gel Corn Remover
NDC: 68016-444 | Form: PATCH
Manufacturer: Chain Drug Consortium, LLC
Category: otc | Type: HUMAN OTC DRUG LABEL
Date: 20241211

ACTIVE INGREDIENTS: SALICYLIC ACID 40 mg/6 1
INACTIVE INGREDIENTS: HIGH DENSITY POLYETHYLENE; VINYL ACETATE; POLYVINYL ALCOHOL, UNSPECIFIED

Premier Value Clear Gel Wart Removers

Active Ingredient

Salicylic acid 40%

Purpose

Wart Remvoer

Uses

- for the removal of common warts. the common wart is easily recognized by the rough 'cauliflower-like' appearance of the surface.

Warnings

For external use only.

Do not use

- if you are diabetic
- have poor blood circulation
- on irritated skin, on any area that is infected or reddened
- on genital warts and warts on the face
- on moles, birthmarks and warts with hair growing from them
- on mucous membranes

Stop use and ask doctor

if discomfort persist

Keep out of reach of children.

If, swallowed , get medical help or cotnact a poison Control Center right away.

Directions

- wash affected area, may soak wart in warm water for 5 minutes
- dry area thoroughly
- if necessary, cut medicated disc to fit wart
- carefully apply adhesive side down of disc onto the wart
- cover disc with cushion to conceal area
- repeart this procedure every 48 hours as needed (until wart is removed) for up to 12 weeks

Other Information

store between 59°F to 86°F (15°F to 30°F)

Inactive Ingredients

acrylic adhesive, acrylic polymer, polyethylene, polyvinyl alcohol

Questions

Call 1-866-964-0939

Principal Display Panel

Premier Value

Medicated

Clear Gel Wart Removers

SALICYLIC ACID 40%

Maximum strength

- Effective wart removal treatment
- Clear gel cushions affected area
- Thin, flexible bandage conceals and protects

9 CUSHIONS

12 MEDICATED DISCS